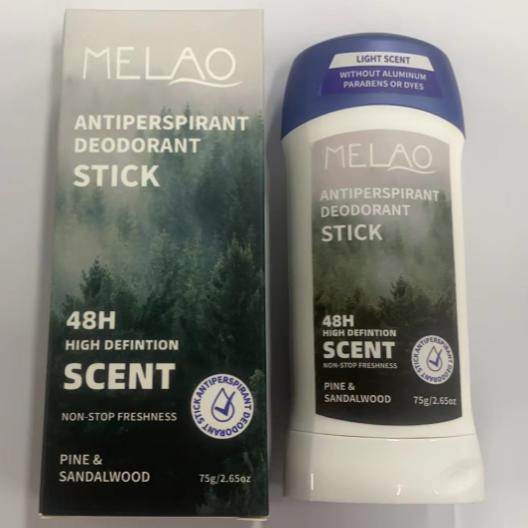 DRUG LABEL: MELAO ANTIPERSPIRANT DEODORANT Stick
NDC: 83566-581 | Form: STICK
Manufacturer: Guangzhou Yilong Cosmetics Co., Ltd
Category: otc | Type: HUMAN OTC DRUG LABEL
Date: 20240820

ACTIVE INGREDIENTS: LIMOSILACTOBACILLUS FERMENTUM 0.93 g/100 g
INACTIVE INGREDIENTS: PARAFFIN 4 g/100 g; 1,3-CYCLOHEXADIENE 2.3 g/100 g; GLYCERYL STEARATE SE 0.5 g/100 g; MAGNESIUM HYDROXIDE 6 g/100 g; PROPYLPARABEN 0.57 g/100 g; ETHYLHEXYL PALMITATE 55 g/100 g; .BETA.-BISABOLOL 0.5 g/100 g; PENTAMETHYL CYCLOPENTASILOXANE 2.4 g/100 g; EFETOZOLE 3.7 g/100 g; PEG-8 BEESWAX 7 g/100 g; COCOS NUCIFERA WHOLE 5 g/100 g; TOCOPHEROL 3.6 g/100 g; AROMADENDRIN 1 g/100 g; BUTYROSPERMUM PARKII (SHEA) BUTTER UNSAPONIFIABLES 5 g/100 g; TRIS-BHT MESITYLENE 2 g/100 g; PEG-6 SORBITAN STEARATE 0.5 g/100 g

MELAO ANTIPERSPIRANT DEODORANT STICK

Active ingredients

Lactobacillus Ferment 0.93%

Inactive ingredients

Ethylhexyl Palmitate 55%

Beeswax 7%

Magnesium Hydroxide 6%

Butyrospermum Parkii (Shea) Butter 5%

Cocos Nucifera (Coconut) Oil 5%

paraffin 4%

Ozokerite 3.70%

Tocopherol 3.60%

Cyclopentasiloxane 2.40%

Cyclohexasiloxane 2.30%

BHT 2%

Aroma 1%

Propylparaben 0.57%

Bisabolol 0.50%

Glyceryl Stearate 0.50%

Sorbitan Stearate 0.50%

Purpose

Deodorization-

Uses

STEP1: Clean and thoroughly dry your skin.

STEP2: Twist the bottom of the product.

STEP3: Gently apply to the underarms or other desired areas.

Warning

For external use only.

Stop use and ask a doctor if

rash occurs.

Do not use

on damaged or broken skin.

When using this product

keep out of eyes. Rinse withwater to remove.

Keep out of reach of children.

If swallowed, get medical help or contact a Poison Control Center right away.

DOSAGE & ADMINISTRATION

Squeeze out an appropriate amount of stick and spread evenly on skin.